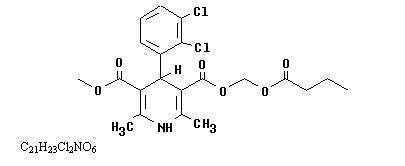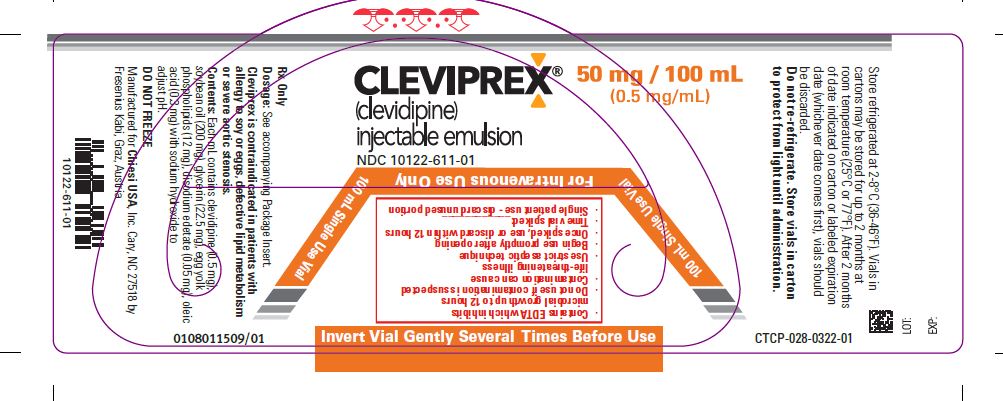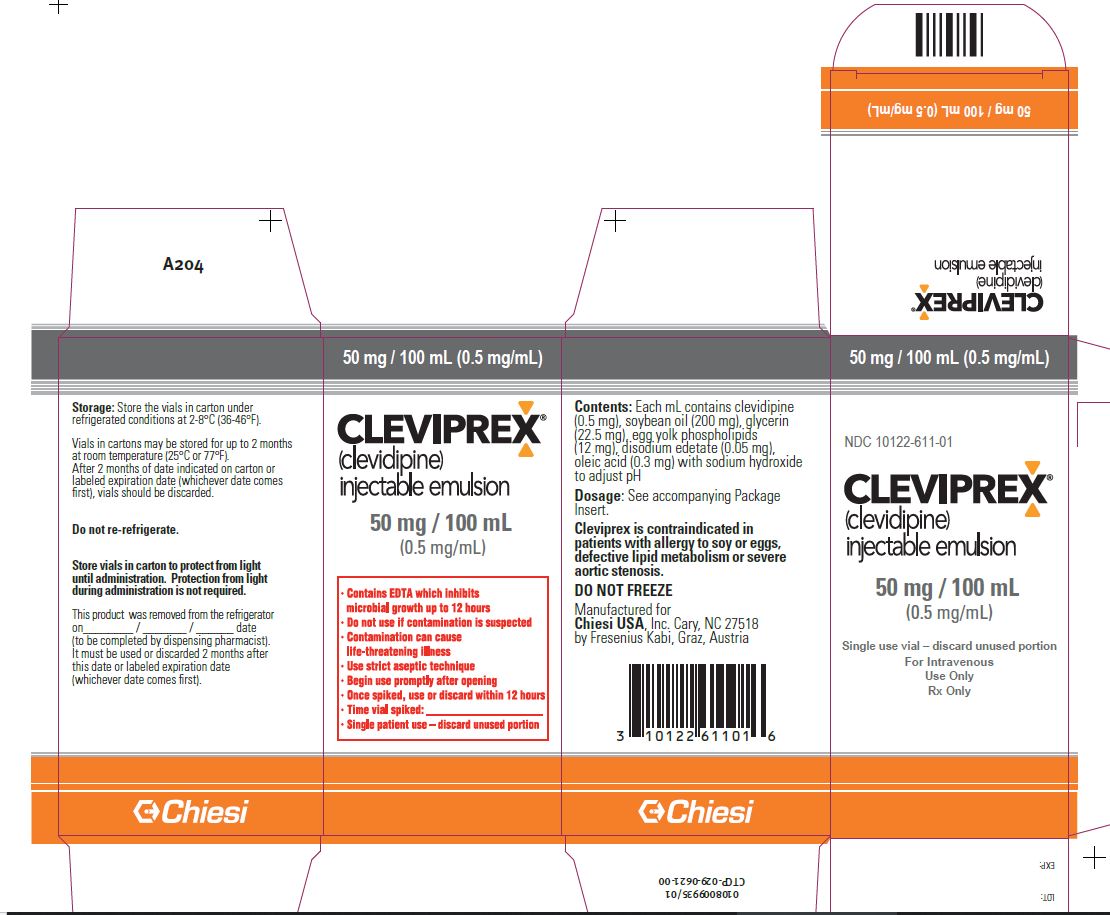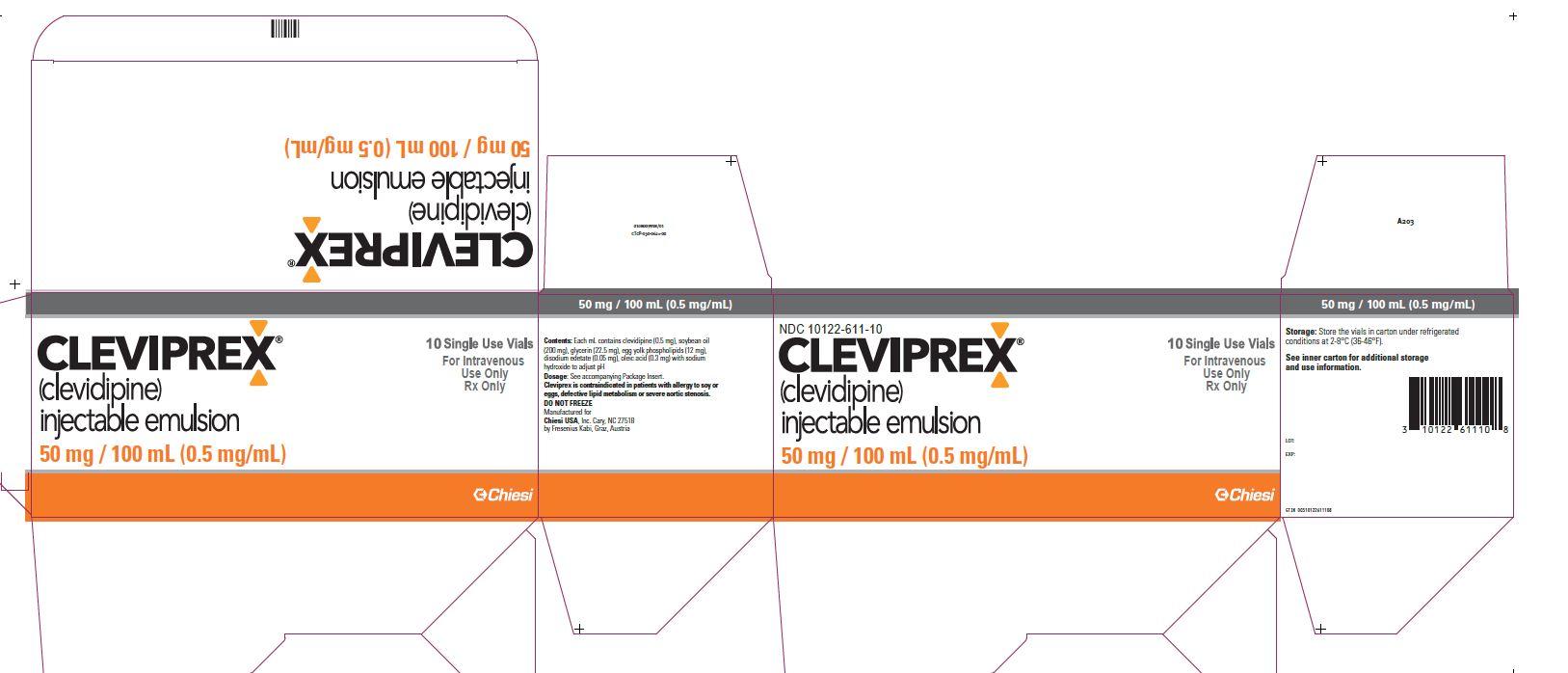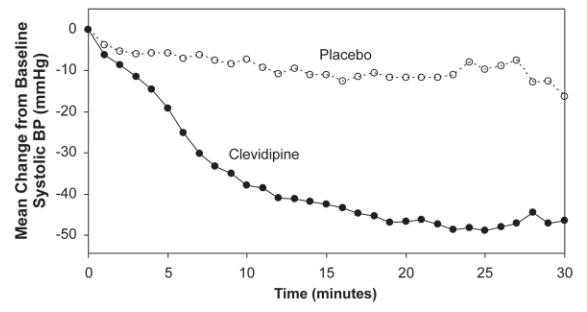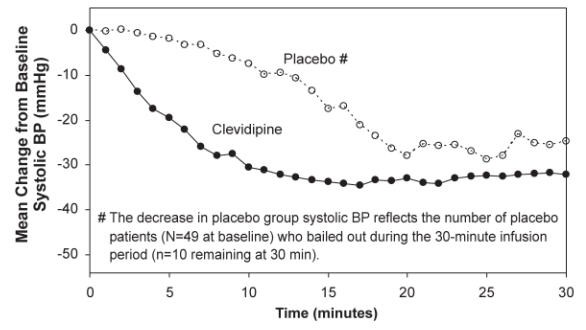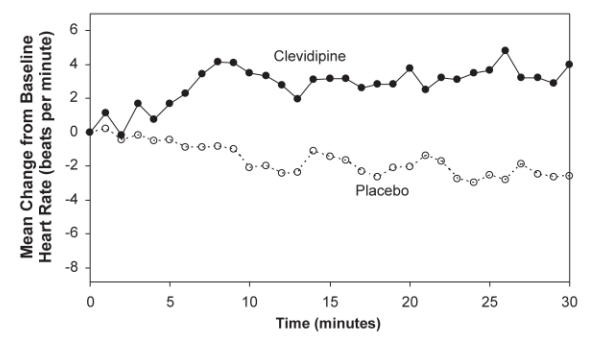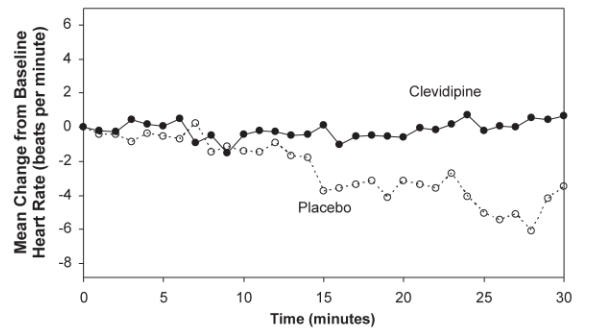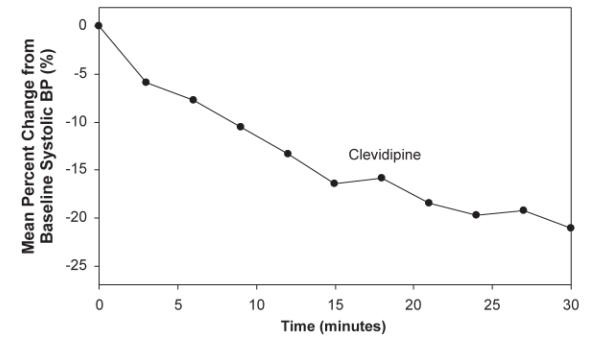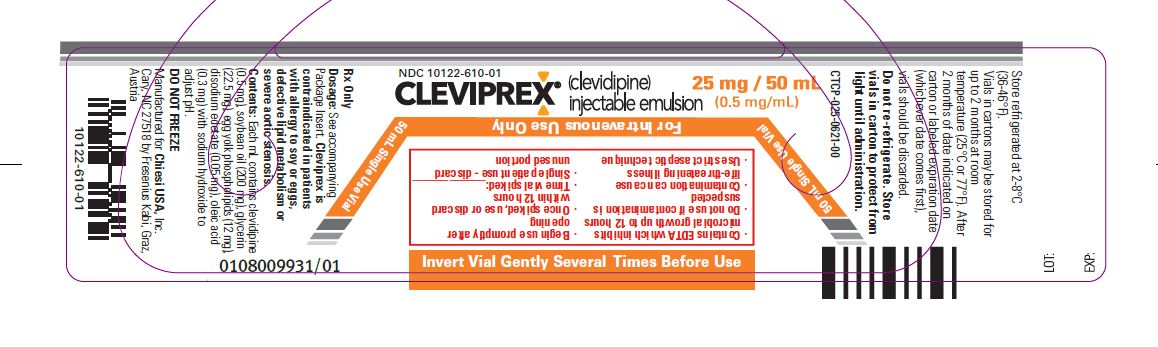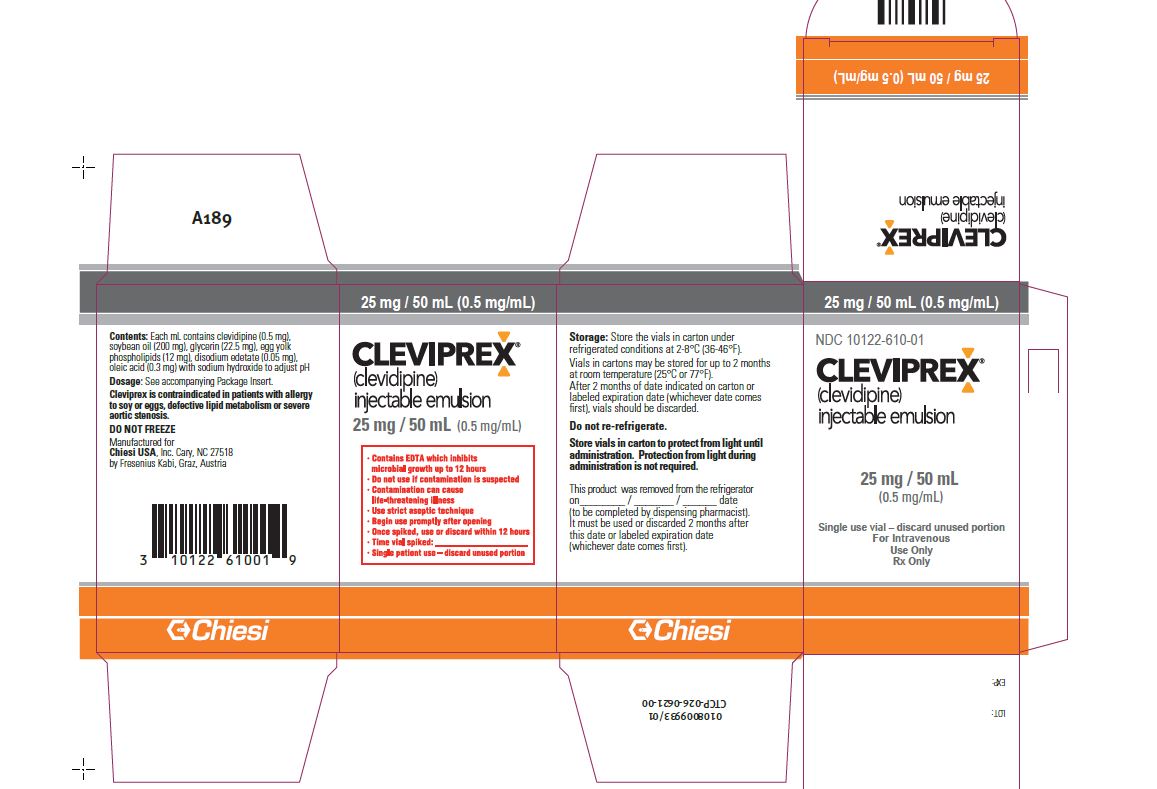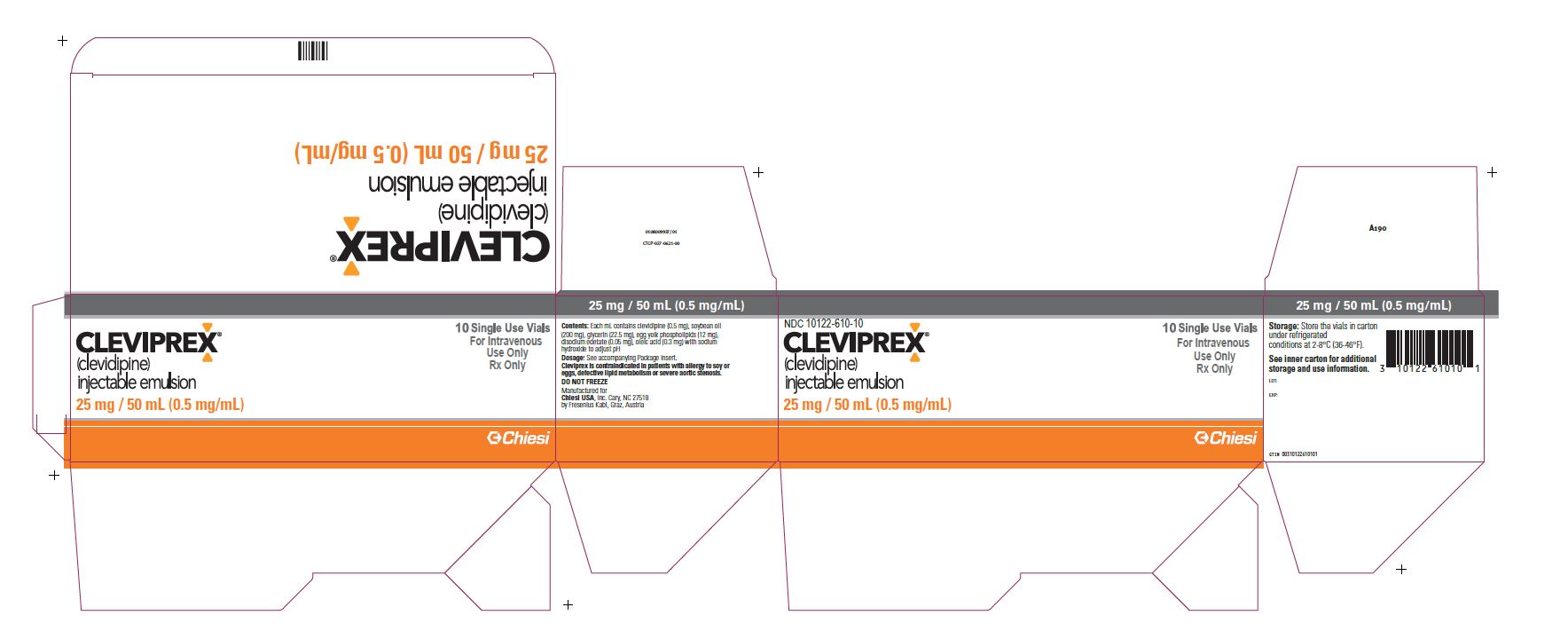 DRUG LABEL: Cleviprex
NDC: 10122-611 | Form: EMULSION
Manufacturer: Chiesi USA, Inc.
Category: prescription | Type: HUMAN PRESCRIPTION DRUG LABEL
Date: 20251106

ACTIVE INGREDIENTS: CLEVIDIPINE 0.5 mg/1 mL
INACTIVE INGREDIENTS: SOYBEAN OIL; GLYCERIN; EGG PHOSPHOLIPIDS; OLEIC ACID; EDETATE DISODIUM; SODIUM HYDROXIDE

HIGHLIGHTS OF PRESCRIBING INFORMATION

These highlights do not include all the information needed to use Cleviprex safely and effectively. See full prescribing information for Cleviprex.
Cleviprex (clevidipine) injectable emulsion, for intravenous use
Initial U.S. Approval: 2008

1 INDICATIONS AND USAGE

Cleviprex is a dihydropyridine calcium channel blocker indicated for the reduction of blood pressure when oral therapy is not feasible or not desirable. (1)

2 DOSAGE AND ADMINISTRATION

For intravenous use: Cleviprex is intended for intravenous use. Titrate Cleviprex to achieve the desired blood pressure reduction. Individualize dosage depending on the blood pressure response of the patient and the goal blood pressure. (2.2)
Monitoring: Monitor blood pressure and heart rate during infusion, and until vital signs stabilize. (2.1)
Initial dose: Initiate intravenous infusion of Cleviprex at 1- 2 mg/hour. (2.2)
Dose titration: Double the dose at short (90 second) intervals initially. As the blood pressure approaches goal, increase the dose by less than doubling and lengthen the time between dose adjustments to every 5-10 minutes. An approximately 1-2 mg/hour increase will generally produce an additional 2-4 mmHg decrease in systolic pressure. (2.2)
Maintenance dose: Most patients will achieve the desired therapeutic response at approximately 4-6 mg/hour. Severe hypertension is likely to require higher doses. (2.2)
Maximum dose: Most patients have received maximum doses of 16 mg/hour or less. There is limited experience with short-term dosing as high as 32 mg/hour. Because of lipid load restrictions, no more than 1000 mL or an average of 21 mg/hour of Cleviprex infusion is recommended per 24 hour period. There is little experience beyond 72 hours at any dose. (2.2)

3 DOSAGE FORMS AND STRENGTHS

Injectible Emulsion. Single-use vials. 50 mL or 100 mL. Concentration is 0.5 mg/mL. (3)

4 CONTRAINDICATIONS

Cleviprex is contraindicated in patients with:

- Allergy to soy or eggs (4.1)
- Defective lipid metabolism (4.2)
- Severe aortic stenosis (4.3)

5 WARNINGS AND PRECAUTIONS

- Maintain aseptic technique. Discard unused portion 12 hours after stopper puncture. (5.1)
- Hypotension and reflex tachycardia are potential consequences of rapid upward titration of Cleviprex. (5.2)
- Dihydropyridine calcium channel blockers can produce negative inotropic effects and exacerbate heart failure. Monitor heart failure patients carefully. (5.4)
- Cleviprex gives no protection against the effects of abrupt beta-blocker withdrawal. (5.5)
- Patients who receive prolonged Cleviprex infusions and are not transitioned to other antihypertensive therapies should be monitored for the possibility of rebound hypertension for at least 8 hours after the infusion is stopped. (5.6)

6 ADVERSE REACTIONS

Most common adverse reactions (>2%) are headache, nausea, and vomiting. (6.1)

To report SUSPECTED ADVERSE REACTIONS, contact Chiesi USA, Inc. at 1-888-661-9260 or FDA at 1-800-FDA-1088 or www.fda.gov/medwatch.

8 USE IN SPECIFIC POPULATIONS

Pediatric use: Safety and effectiveness of Cleviprex in children under 18 years of age have not been established. (8.4)

FULL PRESCRIBING INFORMATION

1 INDICATIONS AND USAGE

Cleviprex is indicated for the reduction of blood pressure when oral therapy is not feasible or not desirable.

2 DOSAGE AND ADMINISTRATION

2.1 Monitoring

Monitor blood pressure and heart rate continually during infusion, and then until vital signs are stable. Patients who receive prolonged Cleviprex infusions and are not transitioned to other antihypertensive therapies should be monitored for the possibility of rebound hypertension for at least 8 hours after the infusion is stopped. These patients may need follow-up adjustments in blood pressure control.

2.2 Recommended Dosing

Cleviprex is intended for intravenous use. Titrate drug to achieve the desired blood pressure reduction. Individualize dosage depending on the blood pressure to be obtained and the response of the patient.

Initial dose: Initiate the intravenous infusion of Cleviprex at 1-2 mg/hour.

Dose titration: The dose may be doubled at short (90 second) intervals initially. As the blood pressure approaches goal, the increase in doses should be less than doubling and the time between dose adjustments should be lengthened to every 5-10 minutes. An approximately 1-2 mg/hour increase will generally produce an additional 2-4 mmHg decrease in systolic pressure.

Maintenance dose: The desired therapeutic response for most patients occurs at doses of 4-6 mg/hour. Patients with severe hypertension may require doses up to 32 mg/hour, but there is limited experience at this dose rate.

Maximum dose: Most patients were treated with maximum doses of 16 mg/hour or less.There is limited short-term experience with doses up to 32 mg/hour. Because of lipid load restrictions, no more than 1000 mL or an average of 21 mg/hour of Cleviprex infusion is recommended per 24 hour period. In clinical trials, 55 hypertensive patients were treated with >500mL of Cleviprex infusion per 24 hour period. There is little experience with infusion durations beyond 72 hours at any dose.

Transition to an oral antihypertensive agent: Discontinue Cleviprex or titrate downward while appropriate oral therapy is established. When an oral antihypertensive agent is being instituted, consider the lag time of onset of the oral agent’s effect. Continue blood pressure monitoring until desired effect is achieved.

2.3 Instructions for Administration

Maintain aseptic technique while handling Cleviprex. Cleviprex is a single-use parenteral product. Do not use if contamination is suspected. Once the stopper is punctured, use within 12 hours and discard any unused portion.

Cleviprex is supplied in sterile, pre-mixed, ready-to-use 50 mL or 100 mL vials. Invert vial gently several times before use to ensure uniformity of the emulsion prior to administration. Inspect parenteral drug products for particulate matter and discoloration prior to administration whenever solution and container permit. Administer Cleviprex using an infusion device allowing calibrated infusion rates. Commercially available standard plastic cannulae may be used to administer the infusion. Administer Cleviprex by a central line or a peripheral line.

Cleviprex should not be administered in the same line as other medications.

Cleviprex should not be diluted, but it can be administered with the following:

- Water for Injection, USP
- Sodium Chloride (0.9%) Injection, USP
- Dextrose (5%) Injection, USP
- Dextrose (5%) in Sodium Chloride (0.9%) Injection, USP
- Dextrose (5%) in Ringers Lactate Injection, USP
- Lactated Ringers Injection, USP
- 10% amino acid

3 DOSAGE FORMS AND STRENGTHS

Cleviprex is a sterile, milky white injectable emulsion for intravenous use, available in the following configurations:

- 50 mL single use vial with 0.5 mg/mL clevidipine
- 100 mL single use vial with 0.5 mg/mL clevidipine

4 CONTRAINDICATIONS

4.1 Known Allergy

Cleviprex is contraindicated in patients with allergies to soybeans, soy products, eggs, or egg products.

4.2 Defective Lipid Metabolism

Cleviprex is contraindicated in patients with defective lipid metabolism such as pathologic hyperlipemia, lipoid nephrosis, or acute pancreatitis if it is accompanied by hyperlipidemia.

4.3 Severe Aortic Stenosis

Cleviprex is contraindicated in patients with severe aortic stenosis because afterload reduction can be expected to reduce myocardial oxygen delivery.

5 WARNINGS AND PRECAUTIONS

5.1 Need for Aseptic Technique

Use aseptic technique and discard any unused product within 12 hours of stopper puncture [see Dosage and Administration (2.3)].

5.2 Hypotension and Reflex Tachycardia

Cleviprex may produce systemic hypotension and reflex tachycardia. If either occurs, decrease the dose of Cleviprex. There is limited experience with short-duration therapy with beta-blockers as a treatment for Cleviprex-induced tachycardia. Beta-blocker use for this purpose is not recommended.

5.3 Lipid Intake

Cleviprex contains approximately 0.2 g of lipid per mL (2.0 kcal). Lipid intake restrictions may be necessary for patients with significant disorders of lipid metabolism. For these patients, a reduction in the quantity of concurrently administered lipids may be necessary to compensate for the amount of lipid infused as part of the Cleviprex formulation.

5.4 Negative Inotropy

Dihydropyridine calcium channel blockers can produce negative inotropic effects and exacerbate heart failure. Monitor heart failure patients carefully.

5.5 Beta-Blocker Withdrawal

Cleviprex is not a beta-blocker, does not reduce heart rate, and gives no protection against the effects of abrupt beta-blocker withdrawal. Withdraw beta-blockers only after a gradual reduction in dose.

5.6 Rebound Hypertension

Patients who receive prolonged Cleviprex infusions and are not transitioned to other antihypertensive therapies should be monitored for the possibility of rebound hypertension for at least 8 hours after the infusion is stopped.

5.7 Pheochromocytoma

There is no information to guide use of Cleviprex in treating hypertension associated with pheochromocytoma.

6 ADVERSE REACTIONS

The following risk is discussed elsewhere in the labeling:

- Hypotension and Reflex Tachycardia [see Warnings and Precautions (5.2)]

6.1 Clinical Trials Experience

Cleviprex clinical development included 19 studies, with 99 healthy subjects and 1307 hypertensive patients who received at least one dose of clevidipine (1406 total exposures). Clevidipine was evaluated in 15 studies in hypertensive patients: 1099 patients with perioperative hypertension, 126 with severe hypertension and 82 patients with essential hypertension.

The desired therapeutic response was achieved at doses of 4-6 mg/hour. Cleviprex was infused for <24 hours in the majority of patients (n=1199); it was infused as a continuous infusion in an additional 93 patients for durations between 24 and 72 hours.

Because clinical trials are conducted under widely varying conditions, adverse reaction rates observed in the clinical trials of a drug cannot be directly compared to rates in the clinical trials of another drug and may not reflect the rates observed in practice.

Use in Perioperative Hypertension

The placebo-controlled experience with Cleviprex in the perioperative setting was both small and brief (about 30 minutes). Table 1 shows treatment-emergent adverse reactions and the category of “any common adverse event” in ESCAPE-1 and ESCAPE-2 where the rate on Cleviprex exceeded the rate on placebo by at least 5% (common adverse reactions).

Table 1. Common adverse reactions in placebo-controlled perioperative studies.
 | ESCAPE-1 |  | ESCAPE-2
 | CLV N=53(%) | PBO N=51(%) | CLV N=61(%) | PBO N=49(%)
Any common adverse event | 27 (51%) | 21 (41%) | 32 (53%) | 24 (49%)
Acute renal failure | 5 (9%) | 1 (2%) | -- | --
Atrial fibrillation | -- | -- | 13 (21%) | 6 (12%)
Nausea | -- | -- | 13 (21%) | 6 (12%)

Three randomized, parallel, open-label studies called ECLIPSE, with longer exposure in cardiac surgery patients define the adverse reactions for patients with perioperative hypertension. Each ECLIPSE study compared Cleviprex (n=752) to an active comparator: nitroglycerin (NTG, n=278), sodium nitroprusside (SNP, n=283), or nicardipine (NIC, n=193). The pooled mean maximum dose in these studies was 10 mg/hour and the mean duration of treatment was 8 hours.

There were many adverse events associated with the operative procedure in the clinical studies of Cleviprex and relatively few plausibly related to the drugs used to lower blood pressure. Thus, the ability to differentiate the adverse event profile between treatments is limited. The adverse events observed within one hour of the end of the infusion were similar in patients who received Cleviprex and in those who received comparator agents. There was no adverse reaction that was more than 2% more common on Cleviprex than on the average of all comparators.

Serious Adverse Events and Discontinuation – Perioperative Hypertension Studies
The incidence of adverse events leading to study drug discontinuation in patients with perioperative hypertension receiving Cleviprex was 5.9% versus 3.2% for all active comparators. For patients receiving Cleviprex and all active comparators the incidence of serious adverse events within one hour of drug infusion discontinuation was similar.

Use in Severe Hypertension

The adverse events for patients with severe hypertension are based on an uncontrolled study in patients with severe hypertension (VELOCITY, n=126).

The common adverse reactions for Cleviprex in severe hypertension included headache (6.3%), nausea (4.8%), and vomiting (3.2%). The incidence of adverse events leading to study drug discontinuation for Cleviprex in severe hypertension was 4.8%.

Less Common Adverse Reactions in Patients with Severe or Essential Hypertension

Adverse reactions that were reported in <1% of patients with severe or essential hypertension included:
Cardiac: myocardial infarction, cardiac arrest
Nervous system: syncope
Respiratory: dyspnea

6.2 Post-Marketing and Other Clinical Experience

Because adverse reactions are reported voluntarily from a population of uncertain size, it is not always possible to estimate reliably their frequency or to establish a causal relationship to drug exposure. The following adverse reactions have been identified during post-approval use of Cleviprex: increased blood triglycerides, ileus, hypersensitivity, hypotension, nausea, decreased oxygen saturation (possible pulmonary shunting) and reflex tachycardia.

8 USE IN SPECIFIC POPULATIONS

8.1 Pregnancy

Risk Summary

The available data based on post-marketing reports with Cleviprex use in pregnant women are not sufficient to inform a drug-associated risk for major birth defects, miscarriage, or adverse maternal or fetal outcomes. There are risks to the mother and fetus associated with poorly controlled hypertension in pregnancy (see Clinical Considerations). In animal studies, clevidipine was associated with increased incidences of intrauterine deaths, slightly reduced fetal weight, retarded skeletal development, abortion, and embryo lethality at doses higher than the expected human dose. No evidence of embryo-fetal malformation was found with continuous IV infusion of clevidipine administered to pregnant rats and rabbits during the period of organogenesis
at multiples of 2.8 and 7.6 times the expected human dose of 16 mg/hour respectively (see Data).

The estimated background risk of major birth defects and miscarriage for the indicated population is unknown. All pregnancies have a background risk of major birth defects, loss, and other adverse outcomes. In the U.S. general population, the estimated major birth defects and miscarriage in clinically recognized pregnancies is 2 to 4% and 15 to 20%, respectively.

Clinical Considerations

Disease-associated maternal and/or embryo/fetal risk

Hypertension in pregnancy increases the maternal risk for pre-eclampsia, gestational diabetes, premature delivery, and delivery complications (e.g., need for cesarean section and postpartum hemorrhage). Hypertension increases the fetal risk for intrauterine growth restriction and intrauterine death. Pregnant women with hypertension should be carefully monitored and managed accordingly.

Data
Animal Data

In pregnant rats, clevidipine caused a dose-related increase in mortality, length of gestation, and prolonged parturition at dose levels of 13, 35, and 55 mg/kg/day.

Clevidipine has been shown to cross the placenta in rats. No evidence of embryo-fetal malformation was found with continuous IV infusion of clevidipine during the period of organogenesis at doses up to 13 mg/kg/day in pregnant rats and 35 mg/kg/day in pregnant rabbits (2.8 to 7.6 times the expected human dose of 16 mg/hour). Embryo-fetal toxicity was seen with continuous IV infusion of clevidipine during the period of major embryonic organogenesis at 35 mg/kg/day in pregnant rats and at 55 mg/kg/day in pregnant rabbits (7.6 to 12 times the expected maximum human dose of 16 mg/hour). There was no evidence that clevidipine was teratogenic at the highest dose levels studied in pregnant rats and rabbits.

8.2 Lactation

Risk Summary

There are no data on the presence of clevidipine in human milk, the effects on the breastfed infant, or the effects on milk production.

8.4 Pediatric Use

The safety and effectiveness of Cleviprex in children under 18 years of age have not been established.

8.5 Geriatric Use

Of the 1406 subjects (1307 with hypertension) treated with Cleviprex in clinical studies, 620 were ≥65 years of age and 232 were ≥75 years of age. No overall differences in safety or effectiveness were observed between these and younger patients. Other reported clinical experience has not identified differences in responses between the elderly and younger patients. In general, for an elderly patient doses should be titrated cautiously, usually starting at the low end of the dosing range, reflecting the greater frequency of decreased hepatic, renal or cardiac function, and of concomitant disease or other drug therapy.

10 OVERDOSAGE

There has been no experience of overdosage in human clinical trials. In clinical trials, doses of Cleviprex up to 106 mg/hour or 1153 mg maximum total dose were administered. The expected major effects of overdose would be hypotension and reflex tachycardia.

Discontinuation of Cleviprex leads to a reduction in antihypertensive effects within 5 to 15 minutes [see Clinical Pharmacology (12.2)]. In case of suspected overdosage, Cleviprex should be discontinued immediately and the patient’s blood pressure should be supported.

11 DESCRIPTION

Cleviprex is a sterile, milky-white emulsion containing 0.5 mg/mL of clevidipine suitable for intravenous administration. Clevidipine is a dihydropyridine calcium channel blocker. Chemically, the active substance, clevidipine, is butyroxymethyl methyl 4-(2´,3´-dichlorophenyl)-1,4-dihydro-2,6-dimethyl-3,5-pyridinedicarboxylate. It is a racemic mixture with a molecular weight of 456.3 g/mol. Each enantiomer has equipotent antihypertensive activity. The structure and formula are:

Clevidipine is practically insoluble in water and is formulated in an oil-in-water emulsion. In addition to the active ingredient, clevidipine, Cleviprex contains soybean oil (200 mg/mL), glycerin (22.5 mg/mL), purified egg yolk phospholipids (12 mg/mL), oleic acid (0.3 mg/mL), disodium edetate (0.05 mg/mL), and sodium hydroxide to adjust pH. Cleviprex has a pH of 6.0 – 8.0 and is a ready-to-use emulsion.

12 CLINICAL PHARMACOLOGY

12.1 Mechanism of Action

Clevidipine is a dihydropyridine L-type calcium channel blocker. L-type calcium channels mediate the influx of calcium during depolarization in arterial smooth muscle. Experiments in anesthetized rats and dogs show that clevidipine reduces mean arterial blood pressure by decreasing systemic vascular resistance. Clevidipine does not reduce cardiac filling pressure (pre-load), confirming lack of effects on the venous capacitance vessels.

12.2 Pharmacodynamics

Cleviprex is titrated to the desired reduction in blood pressure. The effect of Cleviprex appears to plateau at approximately 25% of baseline systolic pressure. The infusion rate for which half the maximal effect is observed is approximately 10 mg/hour.

Onset of Effect: In the perioperative patient population, Cleviprex produces a 4-5% reduction in systolic blood pressure within 2-4 minutes after starting a 0.4 mcg/kg/min infusion (approximately 1-2 mg/hr).

Maintenance of Effect: In studies up to 72 hours of continuous infusion, there was no evidence of tolerance or hysteresis.

Offset of Effect: In most patients, full recovery of blood pressure is achieved in 5-15 minutes after the infusion is stopped.

In studies up to 72 hours of continuous infusion, in patients that were not transitioned to other antihypertensive therapies, there was some evidence of rebound hypertension following Cleviprex discontinuation.

Hemodynamics: Cleviprex causes a dose-dependent decrease in systemic vascular resistance.

Heart Rate:An increase in heart rate is a normal response to vasodilation and decrease in blood pressure; in some patients these increases in heart rate may be pronounced [see Warnings and Precautions (5.2)].

Electrophysiologic Effects:In healthy volunteers, clevidipine or its major carboxylic acid metabolite, at therapeutic and supratherapeutic concentrations (approximately 2.8 times steady-state), did not prolong cardiac repolarization.

12.3 Pharmacokinetics

Clevidipine is rapidly distributed and metabolized resulting in a very short half life. The arterial blood concentration of clevidipine declines in a multi-phasic pattern following termination of the infusion. The initial phase half-life is approximately 1 minute, and accounts for 85-90% of clevidipine elimination. The terminal half-life is approximately 15 minutes.

Distribution: Clevidipine is >99.5% bound to proteins in plasma at 37°C. The steady-state volume of distribution was determined to be 0.17 L/kg in arterial blood.

Metabolism and Elimination: Clevidipine is rapidly metabolized by hydrolysis of the ester linkage, primarily by esterases in the blood and extravascular tissues, making its elimination unlikely to be affected by hepatic or renal dysfunction. The primary metabolites are the carboxylic acid metabolite and formaldehyde formed by hydrolysis of the ester group. The carboxylic acid metabolite is inactive as an antihypertensive. This metabolite is further metabolized by glucuronidation or oxidation to the corresponding pyridine derivative. The clearance of the primary dihydropyridine metabolite is 0.03 L/h/kg and the terminal half-life is approximately 9 hours.

In vitro studies show that clevidipine and its metabolite at the concentrations achieved in clinical practice will not inhibit or induce any CYP enzyme.

In a clinical study with radiolabeled clevidipine, 83% of the drug was excreted in urine and feces. The major fraction, 63-74% is excreted in the urine, 7-22% in the feces. More than 90% of the recovered radioactivity is excreted within the first 72 hours of collection.

13 NONCLINICAL TOXICOLOGY

13.1 Carcinogenesis, Mutagenesis, Impairment of Fertility

Clevidipine displayed positive genotoxic potential in vitro in the Ames test, mouse lymphoma thymidine kinase locus assay, and chromosomal aberration assay, but not in vivo in the mouse micronucleus test. Formaldehyde, a metabolite of clevidipine, a known genotoxicant in vitro and a probable human carcinogen, appears to be at least partially responsible for the positive in vitro results. Long-term studies for evaluation of carcinogenic potential have not been performed with clevidipine due to the intended short-term duration of human use. There were no adverse effects on fertility or mating behavior of male rats at clevidipine doses of up to 55 mg/kg/day, approximately equivalent to the maximum recommended human dose (MRHD) of 504 mg/day (21 mg/hour x 24 hours) on a body surface area basis. Female rats demonstrated pseudopregnancy and changes in estrus cycle at doses as low as 13 mg/kg/day (about 1/4th the MRHD); however, doses of up to 55 mg/kg/day did not affect mating performance or fertility.

14 CLINICAL STUDIES

14.1 Perioperative Hypertension

Cleviprex was evaluated in two double-blind, randomized, parallel, placebo-controlled, multicenter trials of cardiac surgery patients—pre-operative use in ESCAPE-1 (n=105) and post-operative use in ESCAPE-2 (n=110). Patients were undergoing coronary artery bypass grafting, with or without valve replacement. Inclusion in ESCAPE-1 required a systolic pressure ≥160 mmHg. In ESCAPE-2, the entry criterion was systolic pressure of ≥140 mmHg within 4 hours of the completed surgery. The mean baseline blood pressure was 178/77 mmHg in ESCAPE -1 and 150/71 mmHg in ESCAPE-2. The population of both studies included 27% females and 47% patients older than age 65.

Cleviprex was infused in ESCAPE-1 preoperatively for 30 minutes, until treatment failure, or until induction of anesthesia, whichever came first. Cleviprex was infused in ESCAPE-2 postoperatively for a minimum of 30 minutes unless alternative therapy was required. The maximum infusion time allowed in the ESCAPE studies was 60 minutes.

In both studies infusion of Cleviprex was started at a dose of 1- 2 mg/hour and was titrated upwards, as tolerated, in doubling increments every 90 seconds up to an infusion rate of 16 mg/hour in order to achieve the desired blood pressure-lowering effect. At doses above 16 mg/hour, increments were 7 mg/hour. The average Cleviprex infusion rate in ESCAPE-1 was 15.3 mg/hour and in ESCAPE-2 it was 5.1 mg/hour. The mean duration of exposure in the same ESCAPE studies was 30 minutes for the Cleviprex-treated patients.

Approximately 4% of Cleviprex-treated subjects in ESCAPE-1 and 41% in ESCAPE-2 were on concomitant vasodilators during the first 30 minutes of Cleviprex administration.

Cleviprex lowered blood pressure within 2-4 minutes. The change in systolic blood pressure over 30 minutes for ESCAPE-1 (preoperative) and ESCAPE-2 (postoperative) are shown in Figure 1 and 2.

Figure 1. Mean change in systolic blood pressure (mmHg) during 30-minute infusion, ESCAPE-1 (preoperative)

Figure 2. Mean change in systolic blood pressure (mmHg) during 30-minute infusion, ESCAPE-2 (postoperative)

The change in heart rate over 30 minutes for ESCAPE-1 (preoperative) and ESCAPE-2 (postoperative) are shown in Figure 3 and 4.

Figure 3. Mean change in heart rate (bpm) during 30-minute infusion, ESCAPE-1 (preoperative)

Figure 4. Mean change in heart rate (bpm) during 30-minute infusion, ESCAPE-2 (postoperative)

In three Phase 3 open-label clinical trials (ECLIPSE), 1512 patients were randomized to receive Cleviprex, nitroglycerin (perioperative hypertension), sodium nitroprusside (perioperative hypertension), or nicardipine (postoperative hypertension), for the treatment of hypertension in cardiac surgery. The mean exposure in the ECLIPSE studies was 8 hours at 4.5 mg/hour for the 752 patients who were treated with Cleviprex. Blood pressure control was assessed by measuring the magnitude and duration of SBP excursions outside the predefined pre- and post-operative SBP target range of 75-145 mmHg and the predefined intra-operative SBP range of 65-135 mmHg. In general, blood pressure control was similar with the four treatments.

14.2 Severe Hypertension

Cleviprex was evaluated in an open-label, uncontrolled clinical trial (VELOCITY) in 126 patients with severe hypertension (SBP >180 mmHg or diastolic blood pressure [DBP] >115 mmHg). Cleviprex infusion was initiated at 2 mg/hour and up-titrated every 3 minutes, doubling up to a maximum dose of 32 mg/hour as required to achieve a prespecified target blood pressure range within 30 minutes (primary endpoint). The transition to oral antihypertensive therapy was assessed for up to 6 hours following cessation of Cleviprex infusion.

The blood pressure effect in this study is shown in Figure 5. The average infusion rate was 9.5 mg/hour. The mean duration of Cleviprex exposure was 21 hours.

Figure 5. Mean percent change in SBP (%) during the first 30 minutes of infusion, VELOCITY (severe hypertension)

Oral antihypertensive therapy was instituted 1 hour prior to the anticipated cessation of Cleviprex infusion. Transition to oral antihypertensive therapy within 6 hours after discontinuing Cleviprex infusion was successful in 91% (115/126) of patients. No patient had IV antihypertensive therapy reinstituted following transition to oral therapy.

14.3 Essential Hypertension

Cleviprex was evaluated in a randomized, placebo-controlled, single-blind, parallel 72-hour continuous infusion study in 61 mild to moderate essential hypertensives. The mean baseline blood pressure was 151/86 mmHg.

Subjects were randomized to placebo or to 2, 4, 8, or 16 mg/hour. Doses above 2 mg/hour were started at 2 mg/hour and force-titrated in 2-fold increments at 3-minute intervals. Blood pressure, heart rate, and blood levels of clevidipine were measured during the infusion period. Blood levels were monitored 1 hour after the infusion was discontinued. Blood pressure and heart rate were monitored for 8 hours and also at 96 hours after the termination of infusion. Systolic blood pressure effect was related to the concentration of clevidipine and plateaued at higher measured concentrations, with the maximal effect estimated at 25% of baseline systolic blood pressure. The estimated infusion rate necessary to achieve half of this maximal effect was approximately 10 mg/hour.

16 HOW SUPPLIED/STORAGE AND HANDLING

Cleviprex (clevidipine) injectable emulsion is supplied as a sterile, milky white liquid emulsion product in single-use glass vials at a concentration of 0.5 mg/mL of clevidipine.

NDC 10122-610-10: 10 Single Use 50 mL Vials
NDC 10122-611-10: 10 Single Use 100 mL Vials

Storage
Leave vials in cartons until use. Clevidipine is photosensitive and storage in cartons protects against photodegradation. Protection from light during administration is not required.

Store vials refrigerated at 2-8°C (36-46°F). Do not freeze. Vials in cartons may be transferred to 25°C (77°F, USP controlled room temperature) for a period not to exceed 2 months. Upon transfer to room temperature, mark vials in cartons “This product was removed from the refrigerator on _/_/_ date. It must be used or discarded 2 months after this date or the labeled expiration date (whichever date comes first).” Do not return to refrigerated storage after beginning room temperature storage.

Handling
Maintain aseptic technique while handling Cleviprex. Cleviprex is a single-use parenteral product that contains 0.005% disodium edetate to inhibit the rate of growth of microorganisms, for up to 12 hours, in the event of accidental contamination. However, Cleviprex can still support the growth of microorganisms, as it is not an antimicrobially preserved product under USP standards. Do not use if contamination is suspected. Once the stopper is punctured, use within 12 hours and discard any unused portion.

Cleviprex inhibits microbial growth for up to 12 hours, as demonstrated by test data for representative USP microorganisms, staphylococcus epidermidis and serratiamarcescens.

17 PATIENT COUNSELING INFORMATION

- Advise patients with underlying hypertension that they require continued follow up for their medical condition, and, if applicable, encourage patients to continue taking their oral antihypertensive medication(s) as directed.
- Advise patients to contact a healthcare professional immediately for any of the following signs of a new hypertensive emergency: neurological symptoms, visual changes, or evidence of congestive heart failure.

Manufactured by:
Fresenius Kabi Austria GmbH, Graz, Austria

Marketed by:
Chiesi USA, Inc.
Cary, NC 27518

For information call: 1-888-661-9260

CLEVIPREX® is a registered trademark of Chiesi Farmaceutici S.p.A.

US Patent 5,856,346
US Patent 5,739,152

US-192-2-SPL